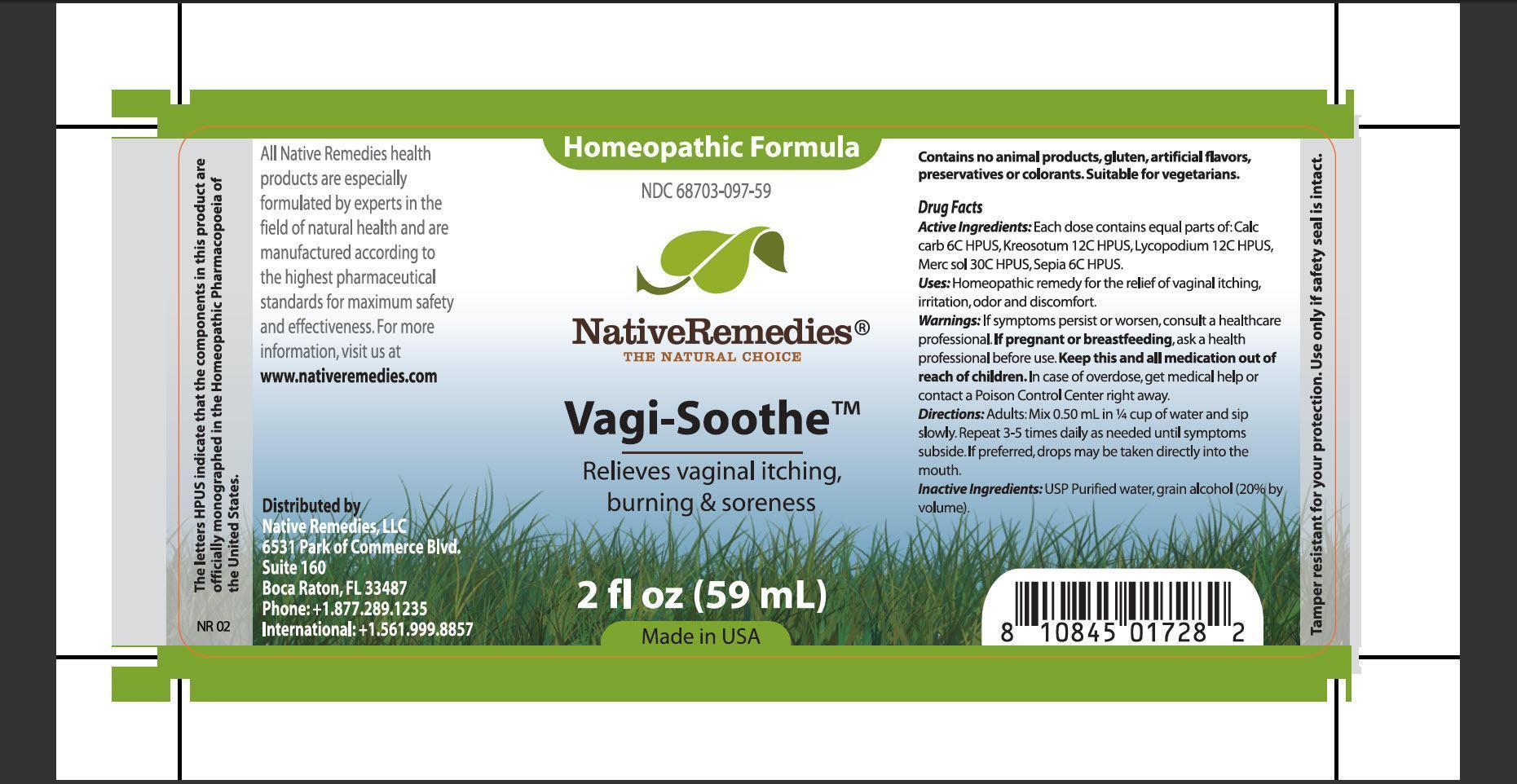 DRUG LABEL: Vagi-Soothe
NDC: 68703-097 | Form: TINCTURE
Manufacturer: Native Remedies, LLC
Category: otc | Type: HUMAN OTC DRUG LABEL
Date: 20130329

ACTIVE INGREDIENTS: OYSTER SHELL CALCIUM CARBONATE, CRUDE 6 [hp_C]/1 mL; WOOD CREOSOTE 12 [hp_C]/1 mL; LYCOPODIUM CLAVATUM SPORE 12 [hp_C]/1 mL; MERCURIUS SOLUBILIS 30 [hp_C]/1 mL; SEPIA OFFICINALIS JUICE 6 [hp_C]/1 mL
INACTIVE INGREDIENTS: WATER; ALCOHOL

Vagi-Soothe

PURPOSE

Relieves vaginal itching, burning and soreness

ACTIVE INGREDIENT

Active Ingredients:Each dose contains equal parts of: Calc carb 6C HPUS, Kreosotum 12C HPUS, Lycopodium 12C HPUS, Merc sol 30C HPUS, Sepia 6C HPUS

INDICATIONS AND USAGE

Uses: Homeopathic remedy for the relief of vaginal itching, irritation, odor and discomfort

WARNINGS

Warning: If symptoms persist or worsen, consult a healthcare professional

PREGNANCY OR BREAST FEEDING

If pregnant of breastfeeding, ask a health professional before use

KEEP OUT OF REACH OF CHILDREN

Keep this and all medication out of reach of children

OVERDOSAGE

In case of overdose, get medical help pr contact a Posion Control Center right away

DOSAGE AND ADMINISTRATION

Directions: Adults: Mix 0.50 mL in 1/4 cup of water and sip slowly. Repeat 3-5 times daily as needed until symptoms subside. If preferred, drops may be taken directly into the mouth

INACTIVE INGREDIENT

Inactive Ingredients: USP Purified water, grain alcohol (20% by volume)

PATIENT COUNSELING INFORMATION

The letters HPUS indicate that the components in this product are officially monographed in the Homeopathic Pharmacopoeia of the United States

All Native Remedies health products are especially formulated by experts in the field of natural health and are manufactured according to the highest pharmaceutical standards for maximum safety and effectiveness. For more information, visit us a www.nativeremedies.com

Distributed by
Native Remedies, LLC
6531 Park of Commerce Blvd.
Suite 160
Boca Raton, Fl 33487
Phone: +1.877.289.1235
International: +1.561.999.8857

Contains no animal products, gluten, artificial flavors, preservatives or colorants. Suitable for vegetarians

STORAGE AND HANDLING

Tamper resistant for your protection. Use only if safety seal is intact